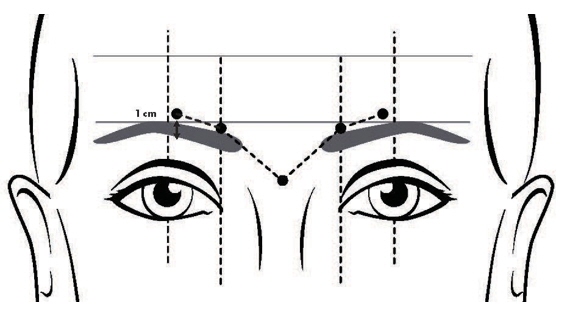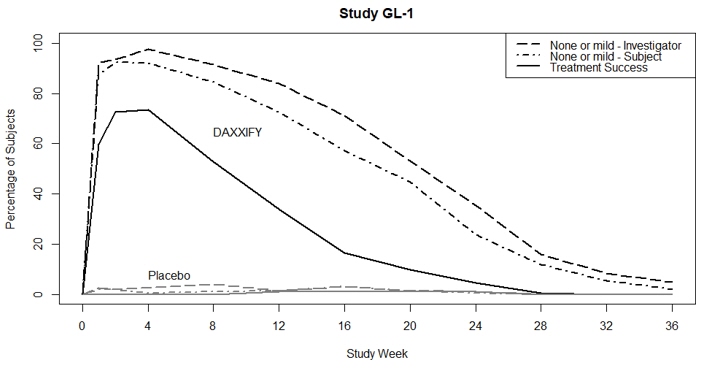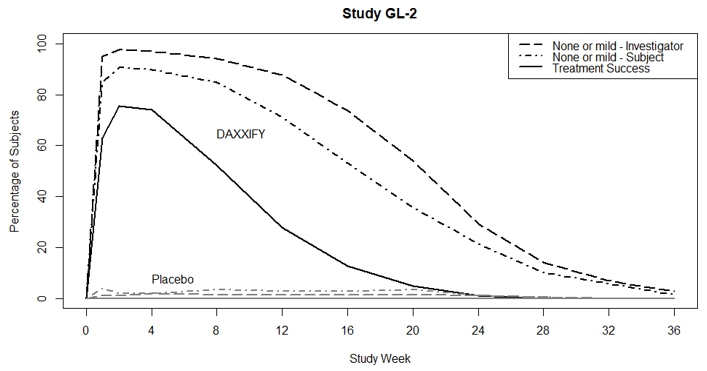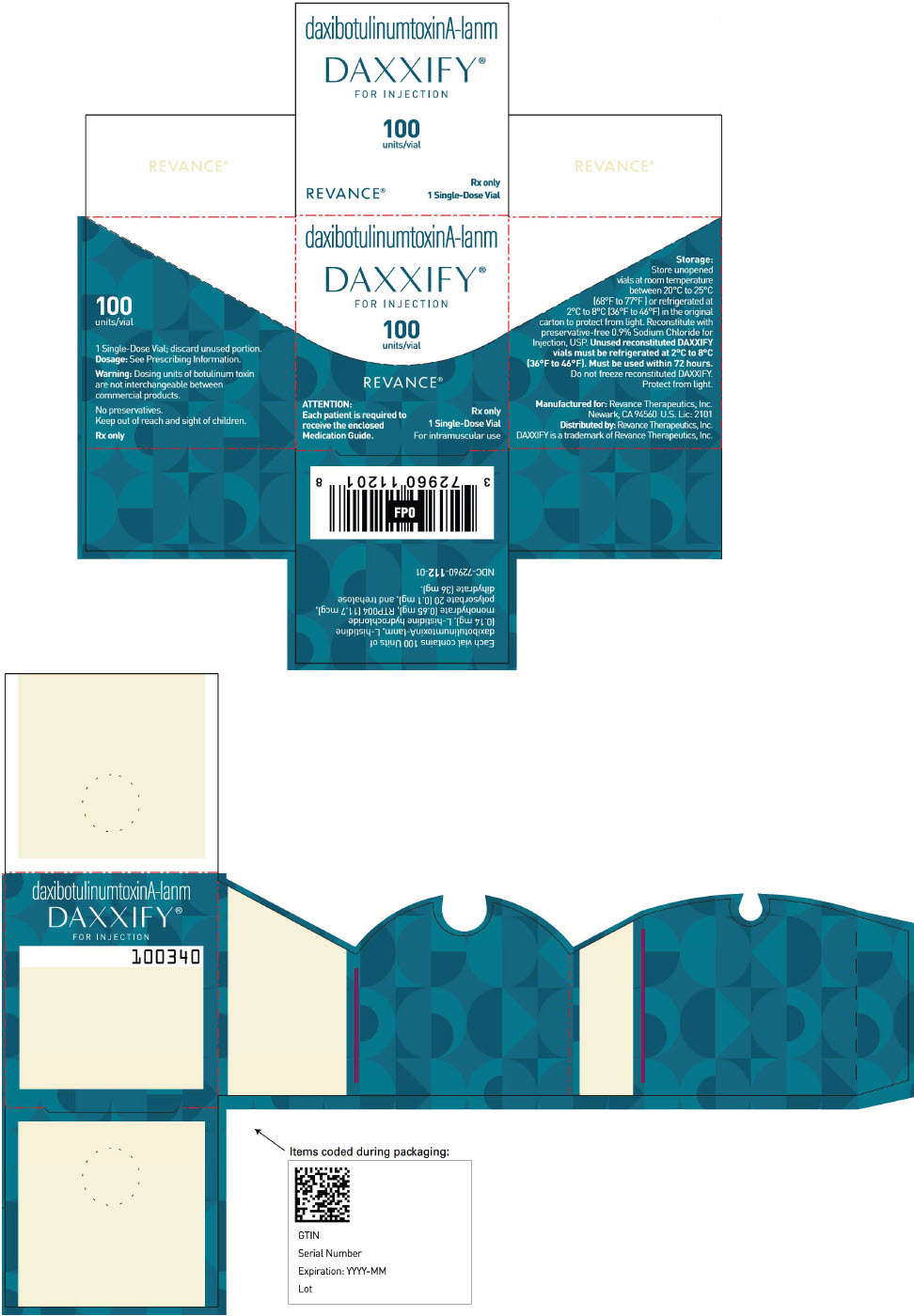 DRUG LABEL: DAXXIFY
NDC: 72960-112 | Form: INJECTION, POWDER, LYOPHILIZED, FOR SOLUTION
Manufacturer: Revance Therapeutics, Inc.
Category: prescription | Type: HUMAN PRESCRIPTION DRUG LABEL
Date: 20260107

ACTIVE INGREDIENTS: BOTULINUM TOXIN TYPE A 100 U/1.2 mL
INACTIVE INGREDIENTS: HISTIDINE 0.14 mg/1.2 mL; TREHALOSE DIHYDRATE 36 mg/1.2 mL; POLYSORBATE 20 0.1 mg/1.2 mL

HIGHLIGHTS OF PRESCRIBING INFORMATION

These highlights do not include all the information needed to use DAXXIFY safely and effectively. See full prescribing information for DAXXIFY.
DAXXIFY ®(daxibotulinumtoxinA-lanm) for injection, for intramuscular use
Initial U.S. Approval: 2022

WARNING: DISTANT SPREAD OF TOXIN EFFECT

See full prescribing information for complete boxed warning.

The effects of DAXXIFY and all botulinum toxin products may spread from the area of injection to produce symptoms consistent with botulinum toxin effects. These symptoms have been reported hours to weeks after injection. Swallowing and breathing difficulties can be life-threatening, and there have been reports of death. The risk of symptoms is probably greatest in children treated for spasticity, an unapproved use for DAXXIFY, but symptoms can also occur in adults, particularly in those patients who have an underlying condition that would predispose them to these symptoms. (5.1)

RECENT MAJOR CHANGES

Boxed Warning | 8/2023
Indications and Usage (1) | 8/2023
Dosage and Administration (2.1,2.3,2.4) | 8/2023
Warnings and Precautions (5.1) | 8/2023

1 INDICATIONS AND USAGE

DAXXIFY is an acetylcholine release inhibitor and neuromuscular-blocking agent indicated for:

- Temporary improvement in the appearance of moderate to severe glabellar lines associated with corrugator and/ or procerus muscle activity in adult patients. (1.1)
- The treatment of cervical dystonia in adult patients. (1.2)

2 DOSAGE AND ADMINISTRATION

Glabellar Lines: the recommended dose is 0.1 mL (8 Units) by intramuscular injection into each of five sites, for a total dose of 40 Units. (2.2)

Cervical Dystonia: the recommended dose is 125 Units to 250 Units given intramuscularly as a divided dose among affected muscles. (2.3)

3 DOSAGE FORMS AND STRENGTHS

For injection: 50 Units or 100 Units sterile lyophilized powder in a single-dose vial. (3)

4 CONTRAINDICATIONS

- Known hypersensitivity to any botulinum toxin preparation, DAXXIFY, or any of the components in the DAXXIFY formulation. (4)
- Infection at the injection sites. (4)

5 WARNINGS AND PRECAUTIONS

- The potency units of DAXXIFY are not interchangeable with other preparations of other botulinum toxin products. (5.2,11)
- Spread of toxin effects, swallowing and breathing difficulties can lead to death. Seek immediate medical attention if respiratory, speech, or swallowing difficulties occur. (5.1)
- Adverse event reports have been received involving the cardiovascular system with botulinum toxin products, some with fatal outcomes. Use caution when administering to patients with pre-existing cardiovascular disease. (5.5)
- Concomitant neuromuscular disorder may exacerbate clinical effects of treatment. (5.6)
- Use with caution in patients with compromised respiratory function or dysphagia. (5.7)
- Potential serious adverse reactions after administration of DAXXIFY for unapproved use. (5.3)

6 ADVERSE REACTIONS

The most commonly observed adverse reactions are:

- Glabellar Lines (≥1%): headache (6%), eyelid ptosis (2%), and facial paresis (1%). (6.1)
- Cervical Dystonia (≥5%): headache (9%), injection site pain (8%), injection site erythema (5%), muscular weakness (5%), and upper respiratory tract infection (5%). (6.1)

To report SUSPECTED ADVERSE REACTIONS, contact Revance Therapeutics, Inc. at 1-877-373-8669 or FDA at 1-800-FDA-1088 or www.fda.gov/medwatch.

7 DRUG INTERACTIONS

Aminoglycoside antibiotics, anticholinergic agents, or any other agents that interfere with neuromuscular transmission may potentiate the effect of DAXXIFY; co-administer only with caution and close observation. (7)

FULL PRESCRIBING INFORMATION

WARNING: DISTANT SPREAD OF TOXIN EFFECT

The effects of all botulinum toxin products, including DAXXIFY, may spread from the area of injection to produce symptoms consistent with botulinum toxin effects. These symptoms have been reported hours to weeks after injection. Swallowing and breathing difficulties can be life-threatening, and there have been reports of death. The risk of symptoms is probably greatest in children treated for spasticity, an unapproved use for DAXXIFY, but symptoms can also occur in adults, particularly in those patients who have an underlying condition that would predispose them to these symptoms[seeWarnings and Precautions (5.1)].

1 INDICATIONS AND USAGE

1.1 Glabellar Lines

DAXXIFY is indicated for the temporary improvement in the appearance of moderate to severe glabellar lines associated with corrugator and/or procerus muscle activity in adult patients.

1.2 Cervical Dystonia

DAXXIFY is indicated for the treatment of cervical dystonia in adult patients.

2 DOSAGE AND ADMINISTRATION

2.1 Important Administration Instructions

The potency units of DAXXIFY for injection are specific to the preparation and test method utilized. They are not interchangeable with other preparations of botulinum toxin products, and, therefore, units of biological activity of DAXXIFY cannot be compared to, or converted into, units of any other botulinum toxin products assessed with any other specific test method[seeWarnings and Precautions (5.2)andDescription (11)].

The safe and effective use of DAXXIFY depends upon proper storage of the product, selection of the correct dose, and proper reconstitution and administration techniques.

DAXXIFY should be administered no more frequently than every three months for any indication. Consideration of the cumulative dose is necessary when treating adult patients with DAXXIFY. Physicians should be aware of whether patients are receiving treatment with other botulinum toxin products for other indications.

Reconstituted DAXXIFY is intended for intramuscular injection only.

After reconstitution, only use each DAXXIFY vial for only one injection session and for only one patient. Discard any remaining solution in vial immediately after administration.

Reconstitution instructions are provided specifically for the 50 Unit and the 100 Unit vials (Table 1; Table 2).

2.2 Recommended Dosage and Administration for Glabellar Lines

Recommended Dosage for Glabellar Lines

The total recommended dose is 40 Units per treatment session divided into five equal intramuscular injections of 8 Units each (two injections in each corrugator muscle and one injection in the procerus muscle).

Administration for Glabellar Lines

Glabellar lines arise from the contraction of the corrugator and procerus muscles. These can be identified by palpation of the glabellar muscle mass while having the patient frown maximally. Contraction of the corrugator muscles compresses the skin, creating a vertical line or lines surrounded by ridges of tensed muscle. Because the exact location, size, and activity of the muscles can vary markedly among individuals, physicians administering DAXXIFY must understand the relevant anatomy of the area involved and any alterations to the anatomy due to prior surgical procedures and diseases[seeWarnings and Precautions (5.3)]. After assessment, the location of the corrugator muscle injection sites may need to be adjusted based on individual facial anatomy and the pattern of muscle contraction.

The upper eyelid margin position should be carefully examined for separation or weakness of the levator palpebrae superioris muscle. Evaluate the range of upper eyelid excursion while manually immobilizing the frontalis to assess degree of levator function and frontalis compensation.

In order to reduce the complication of ptosis, the following steps should be taken:

- Avoid injection near the levator palpebrae superioris, particularly in patients with larger brow depressor complexes.
- Ensure the injected volume/dose is accurate and administer in a steady, controlled manner.
- Do not inject DAXXIFY less than 1 centimeter above the superior orbital rim.

To inject DAXXIFY, clean the exposed portion of the stopper with an alcohol swab and aseptically withdraw at least 0.5 mL of the reconstituted solution from the vial into a sterile syringe. Replace the needle used to withdraw the product with a 30- to 33-gauge sterile needle for injection. Expel any air bubbles prior to administration.

Advance the needle through the skin into the underlying muscle while applying finger pressure on the superior medial orbital rim.

- Inject a dose of 8 Units (0.1 mL) into each of the 5 injection sites: 2 injections into medial corrugator and lateral corrugator muscles respectively, and 1 injection in the procerus muscle (Figure 1).
  FIGURE 1: INJECTION SITES FOR GLABELLAR LINES

2.3 Recommended Dosage for Cervical Dystonia

The recommended dose of DAXXIFY for the treatment of cervical dystonia ranges from 125 Units to 250 Units given intramuscularly as a divided dose among affected muscles. In patients previously treated with another botulinum toxin, their past dose, response to treatment, duration of effect, and adverse event history should be taken into consideration when determining the initial DAXXIFY dose. A description of the average DAXXIFY dose and percentage of total dose injected into specific muscles in the pivotal clinical trials can be found in Section 14. Limiting the dose injected into the sternocleidomastoid muscle may reduce the occurrence of dysphagia.

Dose Modification in Cervical Dystonia

When dose modification is necessary, dose adjustment can be made in 50 to75 Unit increments according to the individual patient's response. The total dose administered in a single treatment is recommended to be between 125 Units and 250 Units.

2.4 Preparation and Dilution Technique

DAXXIFY is supplied in single-dose 50 Unit and 100 Unit vials. Prior to intramuscular injection, reconstitute each vial of DAXXIFY with the required amount of sterile, preservative-free 0.9% Sodium Chloride Injection, USP to obtain a reconstituted solution at the appropriate concentration described in Tables 1 and 2.

TABLE 1: DAXXIFY 50 Unit Vials Dilution Volume for Reconstitution
Indication | Diluent [Preservative-free 0.9% Sodium Chloride Injection, USP] Added to 50 Unit Vial | Resulting Dose in Units per 0.1 mL
Glabellar Lines, Adults | 0.6 mL | 8 Units

TABLE 2: DAXXIFY 100 Unit Vials Dilution Volume for Reconstitution
Indication | Diluent [Preservative-free 0.9% Sodium Chloride Injection, USP] Added to 100 Unit Vials | Resulting Dose in Units per 0.1 mL
Glabellar Lines, Adults | 1.2 mL | 8 Units
Cervical Dystonia, Adults | 1 mL or 2 mL | 10 Units or 5 Units

Slowly inject the diluent into the vial. Discard the vial if a vacuum does not pull the diluent into the vial. Dispose of any unused diluent. Gently mix DAXXIFY with 0.9% Sodium Chloride Injection, USP by rotating the vial.

Reconstituted DAXXIFY solution is clear to slightly opalescent and colorless and free of particulate matter. Inspect visually the reconstituted DAXXIFY for particulate matter and discoloration prior to administration. Do not use if the solution is cloudy or discolored or contains flakes or particles.

Administer DAXXIFY within 72 hours after reconstitution. During this time period, store unused reconstituted DAXXIFY in a refrigerator between 2°C to 8°C (36°F to 46°F) and protected from light. Do not freeze reconstituted DAXXIFY. Dispose of any unused DAXXIFY.

3 DOSAGE FORMS AND STRENGTHS

For injection: 50 Units or 100 Units of white to off-white lyophilized powder in single-dose vial for reconstitution with sterile preservative-free 0.9% Sodium Chloride Injection, USP.

4 CONTRAINDICATIONS

DAXXIFY is contraindicated in:

- patients with known hypersensitivity to any botulinum toxin preparation, DAXXIFY, or any of the components in the DAXXIFY formulation[seeWarnings and Precautions (5.4)].
- the presence of infection at the proposed injection sites.

5 WARNINGS AND PRECAUTIONS

5.1 Spread of Toxin Effect

Postmarketing safety data from other approved botulinum toxins suggest that botulinum toxin effects may be observed beyond the site of local injection. The symptoms are consistent with the mechanism of action of botulinum toxin and may include asthenia, generalized muscle weakness, diplopia, blurred vision, ptosis, dysphagia, dysphonia, dysarthria, urinary incontinence, and breathing difficulties. These symptoms have been reported hours to weeks after injection. Swallowing and breathing difficulties can be life-threatening, and there have been reports of death related to the spread of toxin effects. The risk of symptoms is greatest in children treated for spasticity, an unapproved use for DAXXIFY, but symptoms can occur in adults treated for spasticity and other conditions, and particularly in those patients who have underlying conditions that would predispose them to these symptoms. In unapproved uses, including upper limb spasticity in children, and approved indications, symptoms consistent with spread of toxin effect have been reported at doses comparable to, or lower than, the maximum recommended total dose. Patients or caregivers should be advised to seek immediate medical care if swallowing, speech, or respiratory difficulties occur.

5.2 Lack of Interchangeability between Botulinum Toxin Products

The potency units of DAXXIFY are specific to the preparation and assay method utilized. They are not interchangeable with other preparations of botulinum toxin products; therefore, units of biological activity of DAXXIFY cannot be compared to or converted to units of any other botulinum toxin products assessed with any other specific assay method[seeDescription (11)].

5.3 Serious Adverse Reactions with Unapproved Use

Serious adverse reactions, including excessive weakness, dysphagia, and aspiration pneumonia, with some adverse reactions associated with fatal outcomes, have been reported in patients who received botulinum toxin injections for unapproved uses. In these cases, the adverse reactions may have resulted from the administration of botulinum toxin products to the site of injection and/or adjacent structures. In some cases, patients had pre-existing dysphagia or other significant disabilities. There is insufficient information to identify factors associated with an increased risk for adverse reactions associated with the unapproved uses of botulinum toxin products.

5.4 Hypersensitivity Reactions

Serious and/or immediate hypersensitivity reactions have been reported for botulinum toxin products. These reactions include anaphylaxis, serum sickness, urticaria, soft tissue edema, and dyspnea. If such a reaction occurs, discontinue further injection of DAXXIFY and immediately institute appropriate medical therapy. The use of DAXXIFY in patients with a known hypersensitivity to any botulinum toxin preparation, DAXXIFY, or any of its formulation components could lead to a life-threatening allergic reaction[seeContraindications (4)].

5.5 Cardiovascular System Adverse Reactions

There have been reports following administration of botulinum toxins of adverse events involving the cardiovascular system, including arrhythmia and myocardial infarction, some with fatal outcomes. Some of these patients had risk factors, including pre-existing cardiovascular disease. Use caution when administering to patients with pre-existing cardiovascular disease.

5.6 Increased Neuromuscular Compromise in Patients with Pre-Existing Neuromuscular Disorders

Monitor patients with peripheral motor neuropathic diseases, amyotrophic lateral sclerosis, or neuromuscular junctional disorders (e.g., myasthenia gravis or Lambert-Eaton syndrome) for increased neuromuscular compromise following botulinum toxin treatment. Patients with neuromuscular disorders may be at increased risk of clinically significant effects, including generalized muscle weakness, diplopia, ptosis, dysphonia, dysarthria, severe dysphagia, and respiratory compromise from typical doses of DAXXIFY.

5.7 Dysphagia and Breathing Difficulties

Treatment with botulinum toxin products, including DAXXIFY, can result in swallowing or breathing difficulties. These reactions can occur within hours to weeks after injection with botulinum toxin. Patients with pre-existing swallowing or breathing difficulties may be more susceptible to these complications. In most cases, this is a consequence of weakening of muscles in the area of injection that are involved in breathing or swallowing. When distant effects occur, additional respiratory mechanisms may be involved[seeWarnings and Precautions (5.3)].

Deaths as a complication of severe dysphagia have been reported after treatment with botulinum toxin products. Dysphagia may persist for several months. Aspiration may result from severe dysphagia and is a particular risk when treating patients in whom swallowing or respiratory function is already compromised. Treatment with botulinum toxins, including DAXXIFY, may weaken neck muscles that serve as accessory muscles of ventilation. This may result in a critical loss of breathing capacity in patients with respiratory disorders who may have become dependent upon these accessory muscles. There have been postmarketing reports from other botulinum toxin products of serious breathing difficulties, including respiratory failure.

Patients treated with botulinum toxin may require immediate medical attention should they develop problems with swallowing, speech, or respiratory disorders.

5.8 Facial Anatomy in the Treatment of Glabellar Lines

Use caution when administering DAXXIFY to patients with surgical alterations to the facial anatomy, marked facial asymmetry, excessive dermatochalasis, deep dermal scarring, thick sebaceous skin, inflammation at the injection site(s), pre-existing eyelid or eyebrow ptosis, when excessive weakness or atrophy is present in the target muscles, or the inability to substantially lessen glabellar lines even by physically spreading them apart.

5.9 Ophthalmic Adverse Reactions in Patients Treated for Glabellar Lines

Dry eye has been reported with the use of botulinum toxin products in the treatment of glabellar lines. Reduced tear production, reduced blinking, and corneal disorders may occur with use of botulinum toxins, including DAXXIFY. If symptoms of dry eye (e.g., eye irritation, photophobia, or visual changes) persist, consider referring patient to an ophthalmologist.

6 ADVERSE REACTIONS

The following clinically significant adverse reactions are discussed in greater detail in other sections of the labeling:

- Spread of Toxin Effect[seeWarnings and Precautions (5.1)]
- Hypersensitivity Reactions[seeWarnings and Precautions (5.4)]
- Cardiovascular System Adverse Reactions[seeWarnings and Precautions (5.5)]
- Increased Neuromuscular Compromise in Patients with Pre-Existing Neuromuscular Disorders[seeWarnings and Precautions (5.6)]
- Dysphagia and Breathing Difficulties[seeWarnings and Precautions (5.7)]
- Ophthalmic Adverse Reactions in Patients Treated for Glabellar Lines[seeWarnings and Precautions (5.9)]

6.1 Clinical Trial Experience

Because clinical trials are conducted under widely varying conditions, adverse reaction rates observed in the clinical trials of a drug cannot be directly compared to rates in the clinical trials of another drug and may not reflect the rates observed in practice. The most common side effects from treatment with DAXXIFY usually occur within one to two weeks after injection and, while generally transient, may have a duration of several weeks or months.

Glabellar Lines

In the two randomized, placebo-controlled, Phase 3 clinical trials that assess the use of DAXXIFY for the temporary improvement in the appearance of moderate to severe glabellar lines, GL-1 and GL-2, 406 subjects received a single-dose treatment of 40 Units DAXXIFY, and 203 subjects received placebo.

The most frequent adverse reactions are presented in Table 3.

TABLE 3: Most Common Adverse Reactions ≥1% and More Frequent than Placebo in Pooled Double- Blind, Placebo-Controlled Trials for Glabellar Lines
Adverse Reaction | DAXXIFY N=406 n (%) | Placebo N=203 n (%)
Headache | 26 (6%) | 4 (2%)
Eyelid ptosis | 9 (2%) | 0 (0%)
Facial paresis [Facial paresis, including facial asymmetry.] | 5 (1%) | 0 (0%)

Injection site reactions were reported in 6% of subjects treated with DAXXIFY and in 6% of subjects treated with placebo (these reactions included injection site pain, injection site erythema, injection site oedema, injection site bruising, injection site hematoma, injection site papule, and injection site pruritus).

In an 84-week, open-label, repeat-dose safety study in glabellar lines, 2691 subjects were treated with 40 Units of DAXXIFY. Of these, 2380 subjects received one treatment with DAXXIFY, 882 received two treatments with DAXXIFY, and 568 subjects received three treatments with DAXXIFY. Adverse reactions were reported in 535 of the 2691 subjects (20%). The adverse reaction profile was similar to that reported in single-dose trials.

Injection site reactions were the most common adverse reactions, reported in 9% of subjects [including injection site pain (4%), injection site erythema (3%), injection site oedema (3%), injection site bruising (1%), injection site papule (<1%), and injection site pruritus (<1%)], followed by headache (5%), edema (2%), erythema (2%), and eyelid ptosis in 1% of subjects. The incidence of these adverse reactions did not increase with multiple re- treatments.

Cervical Dystonia

In the randomized, placebo-controlled, Phase 3 clinical trial to assess the use of DAXXIFY for the treatment of cervical dystonia, 255 patients received a dose of DAXXIFY (n=125 for 125 Units and n=130 for 250 Units), and 46 patients received placebo. Table 4 lists adverse reactions that occurred in ≥2% of patients treated with DAXXIFY and more frequently than placebo.

TABLE 4: Most Common Adverse Reactions ≥2% and More Frequent than Placebo in the Phase 3 Double-Blind, Placebo-Controlled Clinical Trial for Cervical Dystonia
Adverse Reaction | DAXXIFY 125 Units N=125 n (%) | DAXXIFY 250 Units N = 130 n (%) | Placebo N=46 n (%)
Headache | 11 (9%) | 9 (7%) | 1 (2%)
Injection site pain | 10 (8%) | 7 (5%) | 2 (4%)
Injection site erythema | 6 (5%) | 3 (2%) | 1 (2%)
Muscular weakness | 6 (5%) | 3 (2%) | 0 (0%)
Musculoskeletal pain | 5 (4%) | 5 (4%) | 0 (0%)
Nasopharyngitis | 4 (3%) | 3 (2%) | 0 (0%)
Arthralgia | 3 (2%) | 1 (1%) | 0 (0%)
Upper respiratory tract infection | 2 (2%) | 7 (5%) | 2 (4%)
Spinal pain | 3 (2%) | 4 (3%) | 1 (2%)
Atrioventricular block first degree | 2 (2%) | 0 (0%) | 0 (0%)
Urinary tract infection | 3 (2%) | 0 (0%) | 0 (0%)
Dysphagia | 2 (2%) | 5 (4%) | 0 (0%)

In a 52-week, open-label, repeat-dose safety study in cervical dystonia, 357 subjects (271 from the randomized trial, 86 newly enrolled) received up to 4 treatments with DAXXIFY. Of these, 28 subjects received one treatment with DAXXIFY, 95 subjects received two treatments, 169 received three treatments, and 65 received four treatments with DAXXIFY.

Adverse reactions were reported in 138 patients (20%).

7 DRUG INTERACTIONS

No formal drug interaction studies have been conducted with DAXXIFY.

However, the potential for certain drugs to potentiate the effects of DAXXIFY warrants consideration given the potential risks involved and should be used with caution.

- Aminoglycosides or other agents interfering with neuromuscular transmission
- Anticholinergic drugs
- Botulinum neurotoxin products
- Muscle relaxants

8 USE IN SPECIFIC POPULATIONS

8.1 Pregnancy

Risk Summary

There are no available data on DAXXIFY use in pregnant women to evaluate for a drug-associated risk of major birth defects, miscarriage, or adverse maternal or fetal outcomes. In animal reproduction studies, intramuscular administration of DAXXIFY during pregnancy resulted in adverse effects on fetal growth (decreased fetal body weight and skeletal ossification) at maternally toxic doses approximately equivalent to 40 times the maximum recommended human dose (MRHD) (seeData).

The background risk of major birth defects and miscarriage for the indicated population is unknown. In the U.S. general population, the estimated background risk of major birth defects and miscarriages in clinically recognized pregnancies is 2-4% and 15-20%, respectively.

Data

Animal Data

Embryofetal development studies were conducted in rats and rabbits with DAXXIFY. For comparison of animal to human doses based on a body weight comparison, the MRHD is set at 40 Units/subject (0.67 Units/kg for an average 60 kg subject).

Intramuscular administration of DAXXIFY (3, 10, or 30 Units/kg) to pregnant rats four times during the period of organogenesis (on gestation days 7, 10, 13, and 16) caused decreased fetal body weight and decreased fetal skeletal ossification at the highest dose, which was associated with maternal toxicity. No embryofetal developmental toxicity was noted at doses up to 10 Units/kg, which is 15 times the MRHD.

Intramuscular administration of DAXXIFY (0.02, 0.1, 0.48, or 2.4 Units/kg/day) to pregnant rabbits during the period of organogenesis (total of 13 doses) resulted in maternal lethality at 2.4 Units/kg/day and significant decreased maternal body weight at 0.48 Units/kg/day. No embryofetal developmental toxicity was noted at doses up to 0.48 Units/kg/day, which is approximately equivalent to the MRHD.

8.2 Lactation

Risk Summary

There are no data on the presence of DAXXIFY in human or animal milk, the effects on the breastfed infant, or the effects on milk production. The developmental and health benefits of breastfeeding should be considered, along with the mother's clinical need for DAXXIFY and any potential adverse effects on the breastfed infant from DAXXIFY or from the underlying maternal condition.

8.4 Pediatric Use

Safety and effectiveness of DAXXIFY in patients less than 18 years of age have not been established.

8.5 Geriatric Use

Glabellar Lines

Among the 406 subjects treated with DAXXIFY in the placebo-controlled clinical trials, 36 subjects were 65 years or older. There was no increase in the incidence of treatment-related adverse events in patients over 65 years treated with DAXXIFY. Clinical studies of DAXXIFY did not include sufficient numbers of subjects aged 65 and older to determine whether they responded differently from younger subjects[seeClinical Studies (14)].

Cervical Dystonia

Among the 255 patients treated with DAXXIFY in the placebo-controlled clinical trial, 83 patients were 65 years or older. There was no increase in the incidence of treatment-related adverse events in patients over 65 years treated with DAXXIFY. Clinical studies of DAXXIFY did not include sufficient numbers of patients aged 65 and older to determine whether they responded differently from younger patients[seeClinical Studies (14)].

10 OVERDOSAGE

Excessive doses of DAXXIFY may be expected to produce neuromuscular weakness with a variety of symptoms. Respiratory support may be required where excessive doses cause paralysis of the respiratory muscles. In the event of overdose, the patient should be medically monitored for symptoms or excessive muscle weakness or muscle paralysis[seeWarnings and Precautions (5.1),(5.7)]. Symptomatic treatment may be necessary.

Symptoms of overdose are not likely to be present immediately following injection. Should accidental injection or oral ingestion occur, the person should be medically supervised for several weeks for signs and symptoms of excessive muscle weakness or paralysis.

In the event of overdose, antitoxin raised against botulinum toxin is available from the Centers for Disease Control and Prevention (CDC) in Atlanta, GA. However, the antitoxin will not reverse any botulinum toxin-induced effects already apparent by the time of antitoxin administration. In the event of suspected or actual cases of botulinum toxin poisoning, please contact your local or state Health Department to process a request for antitoxin through the CDC. If you do not receive a response within 30 minutes, please contact the CDC directly at 1-770-488-7100.

11 DESCRIPTION

DaxibotulinumtoxinA-lanm is an acetylcholine release inhibitor and neuromuscular blocking agent. DaxibotulinumtoxinA-lanm is a 150 kDa botulinum toxin without accessory proteins purified from the bacteriumClostridium botulinumtype A.

DAXXIFY (daxibotulinumtoxinA-lanm) for injection is supplied as a sterile, preservative-free, white to off- white lyophilized powder in a single-dose vial for intramuscular use after reconstitution. DAXXIFY is formulated with a 35 amino acid peptide excipient (RTP004) that prevents surface adsorption and promotes thermal stability of DAXXIFY. Each vial contains 50 Units or 100 Units of daxibotulinumtoxinA-lanm, L- histidine (0.14 mg), L-histidine HCl monohydrate (0.65 mg), polysorbate 20 (0.1 mg), RTP004 peptide (11.7 mcg), and trehalose dihydrate (36 mg).

12 CLINICAL PHARMACOLOGY

12.1 Mechanism of Action

DAXXIFY blocks neuromuscular transmission at the neuromuscular junction by inhibiting the release of acetylcholine. This inhibition occurs as the neurotoxin cleaves SNAP-25, a protein necessary for the successful docking and release of acetylcholine vesicles within nerve endings. Recovery of neurotransmission occurs gradually as the neuromuscular junction recovers from SNAP-25 cleavage and as new nerve endings are formed.

12.2 Pharmacodynamics

No formal pharmacodynamics studies have been conducted with DAXXIFY.

12.3 Pharmacokinetics

Using currently available analytical technology, it is not possible to detect DAXXIFY in the peripheral blood following intramuscular injection at the recommended dose.

12.6 Immunogenicity

The observed incidence of anti-drug antibodies is highly dependent on the sensitivity and specificity of the assay. Differences in assay methods preclude meaningful comparisons of the incidence of anti-drug antibodies in the studies described below with the incidence of anti-drug antibodies in other studies, including those of DAXXIFY.

Glabellar Lines

In the 2786 subjects receiving up to 3 treatments throughout 120 weeks with DAXXIFY in the Phase 3 studies, the incidence of anti-DAXXIFY antibody formation was 0.8% to daxibotulinumtoxinA-lanm and 1.2% to RTP004, the 35 amino acid peptide excipient. No subjects developed neutralizing antibodies to DAXXIFY.

Cervical Dystonia

In the 382 subjects receiving up to 5 treatments throughout 88 weeks with DAXXIFY in the Phase 3 studies, the incidence of anti-DAXXIFY antibody formation was 1.8% to daxibotulinumtoxinA-lanm and 2.4% to RTP004, the 35 amino acid peptide excipient. Two patients who had been previously treated with botulinum toxin tested positive for neutralizing antibodies.

Because of the low occurrence of anti-drug antibodies, the effect of these antibodies on the PK, PD, safety, and/or effectiveness of DAXXIFY products is unknown.

13 NONCLINICAL TOXICOLOGY

13.1 Carcinogenesis, Mutagenesis, Impairment of Fertility

Long-term studies in animals have not been performed to evaluate the carcinogenic potential of DAXXIFY.

Genotoxicity studies have not been conducted for DAXXIFY.

In fertility and early embryonic development studies in rats, intramuscular administration of 3, 10, or 20 Units/kg in males and 3, 10, or 30 Units/kg in females to either male or female rats, respectively, prior to mating and during mating (7 doses, 1 week apart for males; and 4 doses, 1 week apart for females) to untreated animals, caused reduced fertility at doses associated with paternal or maternal toxicity as indicated by reductions in body weight gain and food intake. No effects on fertility were noted at 3 Units/kg in males or at 10 Units/kg in females, which are approximately 4 and 15 times, respectively, the MRHD.

14 CLINICAL STUDIES

14.1 Glabellar Lines

Two randomized, double-blind, multi-center, placebo-controlled clinical trials, Studies GL-1 and GL-2, were conducted to evaluate DAXXIFY for use in the temporary improvement of moderate-to-severe glabellar lines in adults. The 2 trials enrolled a total of 609 subjects (≥18 years old) with glabellar lines of at least moderate severity at maximum frown. A total of 405 subjects were randomized and 406 were treated with 40 Units of DAXXIFY and 204 subjects were randomized and 203 were treated with an equal volume of placebo. Subjects were excluded if they had eyelid ptosis, deep dermal scarring, excessive dermatochalasis, or an inability to lessen glabellar lines by physically spreading them apart. Enrolled subjects were 21 to 75 years old (with a mean age of 50 years), and predominantly female (87%) and Caucasian (86%). The total dose was delivered in 5 equally divided intramuscular injections of 8 Units each to specific sites in the glabella (Figure 1). Subjects were followed for at least 24 weeks after treatment.

Efficacy was determined through the assessment by investigators and subjects of frown wrinkle severity at maximum frown using a 4-point scale (0 = none, 1 = mild, 2 = moderate, 3 = severe). The primary efficacy endpoint (treatment success) was defined as achieving a score of 0 or 1 (none or mild) and an improvement of at least 2 points from baseline for both the investigator's and subject's assessments at Week 4. The percentages of subjects with treatment success at Week 4 are presented in Table 5.

TABLE 5: Percentage of Subjects Achieving a Score of None or Mild and ≥ 2-Grade Improvement from Baseline on the Investigator and Subject Assessment of Glabellar Line Severity at Maximum Frown at Week 4
 | STUDY GL-1 |  |  | STUDY GL-2
 | DAXXIFY (N=201) n (%) | Placebo (N=102) n (%) | Treatment Difference and 95% Confidence Interval | DAXXIFY (N=205) n (%) | Placebo (N=101) n (%) | Treatment Difference and 95% Confidence Interval
Treatment Success [A score of 0 or 1 (none or mild) and ≥ 2-grade improvement from baseline on both the investigator and subject assessment.] | 148 (74%) | 0 (0%) | 74% (68%, 80%) | 152 (74%) | 0 (0%) | 74% (68%, 80%)
Individual Components
Investigator Assessment | 172 (86%) | 1 (1%) | --- | 187 (92%) | 2 (2%) | ---
Subject Assessment | 152 (76%) | 0 (0%) | --- | 156 (77%) | 0 (0%) | ---

Figure 2 shows the proportion of subjects, over 36 weeks, rated as 0 or 1 (none or mild) by the investigator, 0 or 1 by the subject, and 0 or 1 with at least a 2-point improvement from their baseline based on both the investigator and subject ratings. Subjects were followed through at least Week 24 and then were discontinued from the study when both the investigator and subject scores returned to baseline. Subjects who returned to baseline levels prior to Week 36 were counted as non-responders following study discontinuation.

FIGURE 2: Proportion of subjects rated as 0 or 1 (none or mild) by investigator, 0 or 1 by the subject, and 0 or 1 with at least 2-point improvement from their baseline (based on both the investigator and subject ratings) in Study GL-1 and Study GL-2.

Treatment success is defined as a score of 0 or 1 (none or mild) and ≥ 2-grade improvement from baseline on both the investigator and subject assessment.

14.2 Cervical Dystonia

The efficacy of DAXXIFY was evaluated in a randomized, double-blind, placebo-controlled, multi-center trial in a total of 301 patients (NCT03608397). The mean age of patients was 58 years, 65% were women, and 96% were White. At study baseline, 84% of patients had previously received a botulinum toxin as treatment for cervical dystonia. Patients had a clinical diagnosis of cervical dystonia with baseline Toronto Western Spasmodic Torticollis Rating Scale (TWSTRS) total score ≥ 20, TWSTRS severity score ≥15, TWSTRS disability score ≥3, and TWSTRS pain score ≥1. For patients who had previously received a botulinum toxin treatment for cervical dystonia, the trial required that ≥14 weeks had passed since the most recent botulinum toxin administration.

Patients were randomized (3:3:1) to receive a single administration of 2.5 mL of either DAXXIFY 125 Units (n = 125), DAXXIFY 250 Units (n = 130), or placebo (n = 46), divided amongst the affected muscles as selected by the investigator. Table 6 indicates the treated muscles, along with the number of patients treated and DAXXIFY units.

TABLE 6: Summary of Muscles Treated in Each DAXXIFY Treatment Group
Unilateral Muscle Injected | DAXXIFY 125 Units |  | DAXXIFY 250 Units
 | Number of Patients | Median Units (min, max) | Number of Patients | Median Units (min, max)
Levator Scapulae | 106 | 20 (10, 30) | 105 | 50 (20, 60)
Longissimus Capitis and Cervices | 45 | 15 (10, 30) | 58 | 40 (20, 60)
Scalenus Complex | 55 | 15 (10, 15) | 44 | 30 (20, 30)
Splenius Capitis | 120 | 25 (10, 50) | 127 | 50 (20, 100)
Splenius Cervices | 65 | 20 (10, 50) | 71 | 40 (20, 100)
Sternocleidomastoid | 115 | 25 (10, 25) | 121 | 50 (20, 50)
Trapezius | 105 | 20 (15, 40) | 105 | 40 (30, 80)

The primary efficacy endpoint was the mean change in the TWSTRS total score from baseline averaged over weeks 4 and 6. TWSTRS evaluates the severity of dystonia, patient-perceived disability from dystonia, and pain, with a range of possible scores from 0 to 85. The mean change from baseline in the total TWSTRS score was significantly greater for both dosage groups of DAXXIFY than for placebo (Table 7).

TABLE 7: Change in TWSTRS Score Averaged over Weeks 4 and 6 in Patients with Cervical Dystonia
TWSTRS Assessment | Placebo (N = 46) | DAXI 125 Units (N = 125) | DAXI 250 Units (N = 130)
Baseline mean | 45.3 | 43.1 | 42.6
Least squares mean change from baseline | -4.3 | -12.7 | -10.9
Least squares mean difference from placebo (95% CI) |  | -8.4 (-12.2, -4.6) | -6.6 (-10.4, -2.8)
p-value |  | <0.0001 | 0.0007

A similar pattern of significant improvement versus placebo was observed in the clinician global impression of change (CGIC) and patient global impression of change (PGIC) scales.

16 HOW SUPPLIED/STORAGE AND HANDLING

How Supplied

DAXXIFY (daxibotulinumtoxinA-lanm) for injection is a sterile lyophilized powder supplied in a single-dose vial in the following sizes:

Carton containing one 50 Units/Vial NDC 72960-111-01
Carton containing one 100 Units/Vial NDC 72960-112-01

Storage and Handling

Unopened DAXXIFY vials should be stored at room temperature 20°C to 25°C (68°F to 77°F) or refrigerated at 2°C to 8° C (36°F to 46°F) in the original carton to protect from light.

17 PATIENT COUNSELING INFORMATION

Advise the patient to read the FDA-approved patient labeling (Medication Guide).

Swallowing, Speaking, or Breathing Difficulties, or other Unusual Symptoms

Advise patients or caregivers to seek immediate medical care if swallowing, speech, or respiratory disorders arise or existing symptoms worsen[seeWarnings and Precautions (5.1) (5.7)].

Ability to Operate Machinery or Vehicles

Advise patients if they develop any unusual symptoms such as loss of strength, muscle weakness, blurred vision, or drooping eyelids, they should avoid driving a car or engaging in other potentially hazardous activities[seeWarnings and Precautions (5.1)].

Ophthalmic Adverse Reactions

Inform patients that DAXXIFY injection may cause eye dryness. Advise patients to report symptoms of eye dryness (e.g., eye pain, eye irritation, photosensitivity, or changes in vision) to their doctor[seeWarnings and Precautions (5.9)].

Manufactured for:
Revance Therapeutics, Inc. Newark, CA 94560
U.S. License Number 2101

© 2023 Revance Therapeutics, Inc.
DAXXIFY is a registered trademark of Revance Therapeutics, Inc.
PI761127-5.0

MEDICATION GUIDE
DAXXIFY®(dax'-i-fye)
daxibotulinumtoxinA-lanm
for injection, for intramuscular use

What is the most important information I should know about DAXXIFY?
DAXXIFY may cause serious side effects that can be life-threatening. Call your healthcare provider or get medical help right away if you have any of these problems after treatment with DAXXIFY:

- Problems swallowing, speaking, or breathing. These problems can happen hours, days, or weeks after an injection of DAXXIFYif the muscles that you use to breathe and swallow become weak after the injection. Death can happen as a complication if you have severe problems with swallowing or breathing after treatment with DAXXIFY.
  - People with certain breathing problems may need to use muscles in their neck to help them breathe. These people may be at greater risk for serious breathing problems with DAXXIFY.
  - Swallowing problems may last for several months. People who cannot swallow well may need a feeding tube to receive food and water. If swallowing problems are severe, food or liquids may go into your lungs. People who already have swallowing or breathing problems before receiving DAXXIFY have the highest risk of getting these problems.
- Spread of toxin effects. In some cases, the effect of botulinum toxin may affect areas of the body away from the injection site and cause symptoms of a serious condition called botulism. The symptoms of botulism include:

- loss of strength and muscle weakness all over the body
- blurred vision and drooping eyelids
- trouble saying words clearly
- trouble breathing

- double vision
- hoarseness or change or loss of voice
- loss of bladder control
- trouble swallowing

These symptoms can happen hours, days, or weeks after you receive an injection of DAXXIFY.
These problems could make it unsafe for you to drive a car or do other dangerous activities. See "What should I avoid while receiving DAXXIFY?"

What is DAXXIFY?
DAXXIFY is a prescription medicine for adults that is injected into muscles and used:

- to temporarily improve the look of moderate to severe frown lines between the eyebrows (glabellar lines)
- to treat cervical dystonia (CD)

It is not known if DAXXIFY is safe and effective in children less than 18 years of age.

Do not receive DAXXIFY if you:

- are allergic to DAXXIFY or to any of the ingredients in DAXXIFY. See the end of this Medication Guide for a complete list of ingredients in DAXXIFY.
- have had an allergic reaction to any other botulinum toxin product such as rimabotulinumtoxinB (MYOBLOC), onabotulinumtoxinA (BOTOX, BOTOX COSMETIC), abobotulinumtoxinA (DYSPORT), incobotulinumtoxinA (XEOMIN), or prabotulinumtoxinA-xvfs (JEUVEAU).
- have a skin infection at the planned injection site.

Before receiving DAXXIFY, tell your healthcare provider about all of your medical conditions, including if you:

- have a disease that affects your muscles and nerves (such as amyotrophic lateral sclerosis [ALS or Lou Gehrig's disease], myasthenia gravis, or Lambert-Eaton syndrome). See"What is the most important information I should know about DAXXIFY?"
- have had any side effect from any other botulinum toxin in the past.
- have or have had a breathing problem, such as asthma or emphysema.
- have or have had swallowing problems.
- have or have had heart problems.
- have or have had bleeding problems.
- have weakness of your forehead muscles, such as trouble raising your eyebrows.
- have drooping eyelids.
- plan to have surgery.
- have had surgery on your face.
- have had dry eye problems with the use of botulinum toxin products in the past.
- are pregnant or plan to become pregnant. It is not known if DAXXIFY can harm your unborn baby.
- are breastfeeding or plan to breastfeed. It is not known if DAXXIFY passes into your breast milk. Talk to your healthcare provider about the best way to feed your baby during treatment with DAXXIFY.

Tell your healthcare provider about all the medicines you take,including prescription and over-the-counter medicines, vitamins, and herbal supplements.
Using DAXXIFY with certain other medicines may cause serious side effects.Do not start any new medicines until you have told your healthcare provider that you have received DAXXIFY in the past.
Especially tell your healthcare provider if you:

- have received any other botulinum toxin product in the last 4 months.
- have received injections of botulinum toxin such as rimabotulinumtoxinB (MYOBLOC), onabotulinumtoxinA (BOTOX, BOTOX COSMETIC), abobotulinumtoxinA (DYSPORT), prabotulinumtoxinA (JEUVEAU), and incobotulinumtoxinA (XEOMIN) in the past. Be sure your healthcare provider knows exactly which product you received.

Know the medicines you take. Keep a list of your medicines with you to show your healthcare provider and pharmacist each time you get a new medicine.

How will I receive DAXXIFY?

- DAXXIFY is an injection that your healthcare provider will give you.
- DAXXIFY is injected into your affected muscles.
- Your healthcare provider may change your dose of DAXXIFY until you and your healthcare provider find the best dose for you.
- DAXXIFY should not be received more than 1 time every 3 months.
- Your healthcare provider will tell you how often you will receive your dose of DAXXIFY injections.

What should I avoid while receiving DAXXIFY?
DAXXIFY may cause loss of strength or general muscle weakness, blurred vision, or drooping eyelids within hours to weeks of receiving DAXXIFY.If this happens, do not drive a car, operate machinery, or do other dangerous activities.See "What is the most important information I should know about DAXXIFY?"

What are the possible side effects of DAXXIFY? DAXXIFY may cause serious side effects, including:

- See"What is the most important information I should know about DAXXIFY?"
- Allergic reactions.Symptoms of an allergic reaction to DAXXIFY may include itching, rash, redness, swelling, wheezing, trouble breathing, or dizziness or feeling faint. Tell your healthcare provider or get medical help right away if you have wheezing or trouble breathing, or if you feel dizzy or faint.
- Heart problems.Irregular heartbeat and heart attacks that have resulted in death have happened in some people who received botulinum toxin products.
- Eye problems.Dry eye, reduced blinking, and corneal problems have happened in some people who receive DAXXIFY to treat glabellar lines. Tell your healthcare provider if you develop eye pain or irritation, sensitivity to light, or changes in your vision.

The most common side effects of DAXXIFY in people with glabellar lines include:

- headache
- eyelid drooping

- loss of the ability to move the muscles in your face

The most common side effects of DAXXIFY in people with cervical dystonia include:

- headache
- muscle weakness

- injection site pain
- upper respiratory tract infection

- injection site redness

These are not all the possible side effects of DAXXIFY.
Call your doctor for medical advice about side effects. You may report side effects to FDA at 1-800-FDA-1088.
You may also report side effects to Revance Therapeutics, Inc. at 1-877-373-8669.

General information about the safe and effective use of DAXXIFY.
Medicines are sometimes prescribed for purposes other than those listed in a Medication Guide. You can ask your pharmacist or healthcare provider for information about DAXXIFY that is written for health professionals.

What are the ingredients in DAXXIFY?
Active ingredient:daxibotulinumtoxinA-lanm
Inactive ingredients:L-histidine, L-histidine HCl monohydrate, polysorbate 20, RTP004 peptide, trehalose dihydrate
Manufactured by: Revance Therapeutics, Inc. Newark, CA 94560
U.S. License Number 2101
© 2023 Revance Therapeutics, Inc.
All trademarks are the property of their respective owners. MG761127-4.0

This Medication Guide has been approved by the U.S. Food and Drug Administration.

Revised: 11/2023

PRINCIPAL DISPLAY PANEL - 100 Units Vial Carton

daxibotulinumtoxinA-lanm

DAXXIFY®
FOR INJECTION

100
units/vial

REVANCE®

ATTENTION:
Each patient is required to
receive the enclosed
Medication Guide.

Rx only
1 Single-Dose Vial
For intramuscular use